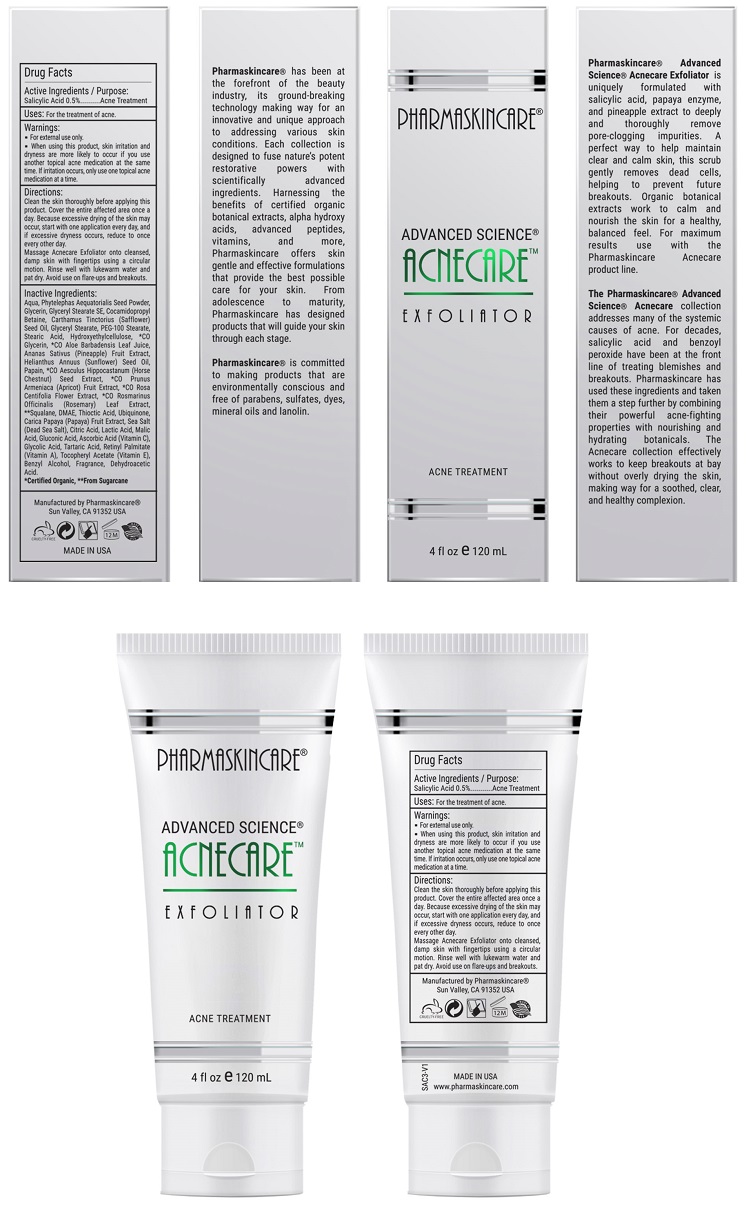 DRUG LABEL: Pharmaskincare Acnecare Exfoliator
NDC: 68062-9110 | Form: SOLUTION
Manufacturer: Spa de Soleil
Category: otc | Type: HUMAN OTC DRUG LABEL
Date: 20171011

ACTIVE INGREDIENTS: SALICYLIC ACID 0.013 mg/2.5 mL
INACTIVE INGREDIENTS: WATER; GLYCERIN; GLYCERYL STEARATE SE; SAFFLOWER OIL; PHYTELEPHAS AEQUATORIALIS SEED

Pharmaskincare Acnecare Exfoliator

Active Ingredient

Salicylic Acid 0.5%

Purpose

Acne Treatment

Warnings

- For external use only.
- When using this product : skin irritation and dryness is more likely to occur if you use another topical acne medication at the same time. If irritation occurs, only use one topical acne medication at a time.

Directions

Clean the skin thoroughly before applying this product. Cover the entire affected area with a thin layer and rinse thoroughly one to three times daily. Because excessive drying of the skin may occur, start with one application daily, then gradually increase to two or three times daily if needed or as directed by a doctor.

Massage Acnecare Exfoliator onto cleansed, damp skin with fingertips using a circular motion. Rinse well with lukewarm water and pat dry. Avoid use on flare-ups and breakouts.

Uses:

For the treatment of acne.

Inactive Ingredients:

Water, Phytelephas Aequatorialis Seed Powder, Glycerin, Glyceryl Stearate SE, Cocamidopropyl Betaine, Carthamus Tinctorius (Safflower) Seed Oil, Glyceryl Stearate, PEG-100 Stearate, Stearic Acid, Hydroxyethylcellulose, *CO Glycerin, *CO Aloe Barbadensis Leaf Juice, Ananas Sativus (Pineapple) Fruit Extract, Helianthus Annuus (Sunflower) Seed Oil, Papain, *CO Aesculus Hippocastanum (Horse Chestnut) Seed Extract, *CO Prunus Armeniaca (Apricot) Fruit Extract, *CO Rosa Centifolia Flower Extract, *CO Rosmarinus Officinalis (Rosemary) Leaf Extract, **Squalane, DMAE, Thioctic Acid, Ubiquinone, Carica Papaya (Papaya) Fruit Extract, Sea Salt (Dead Sea Salt), Malus Domestica Fruit Cell Culture Extract, Xanthan Gum, Citric Acid, Lactic Acid, Malic Acid, Gluconic Acid, Ascorbic Acid (Vitamin C), Lecithin, Glycolic Acid, Tartaric Acid, Tocopheryl Acetate (Vitamin E), Retinyl Palmitate (Vitamin A), Benzyl Alcohol, Fragrance, Dehydroacetic Acid

Warning

Keep out of reach of children.

PACKAGE LABEL

Pharmaskincare AcnecareExfoliator.jpg